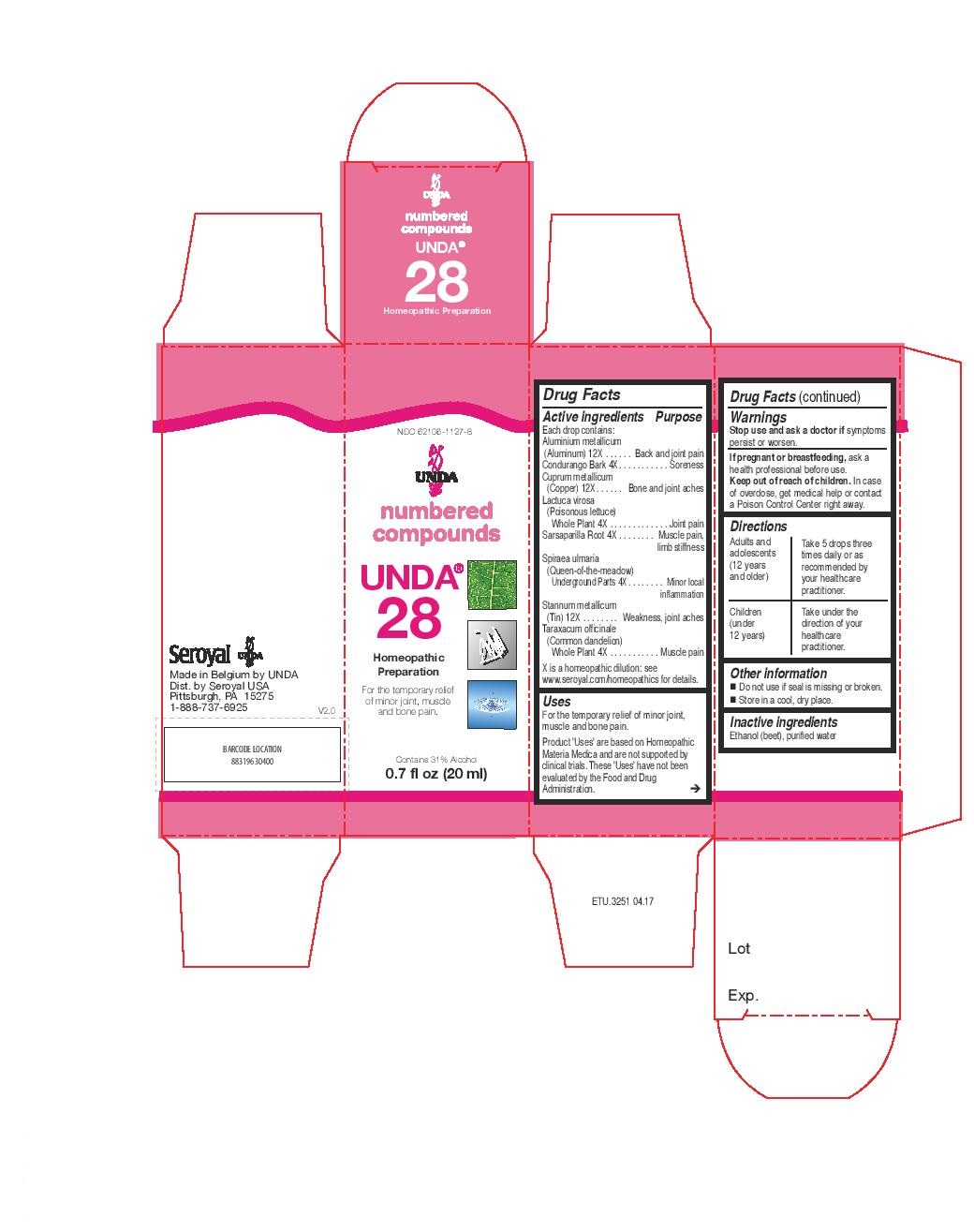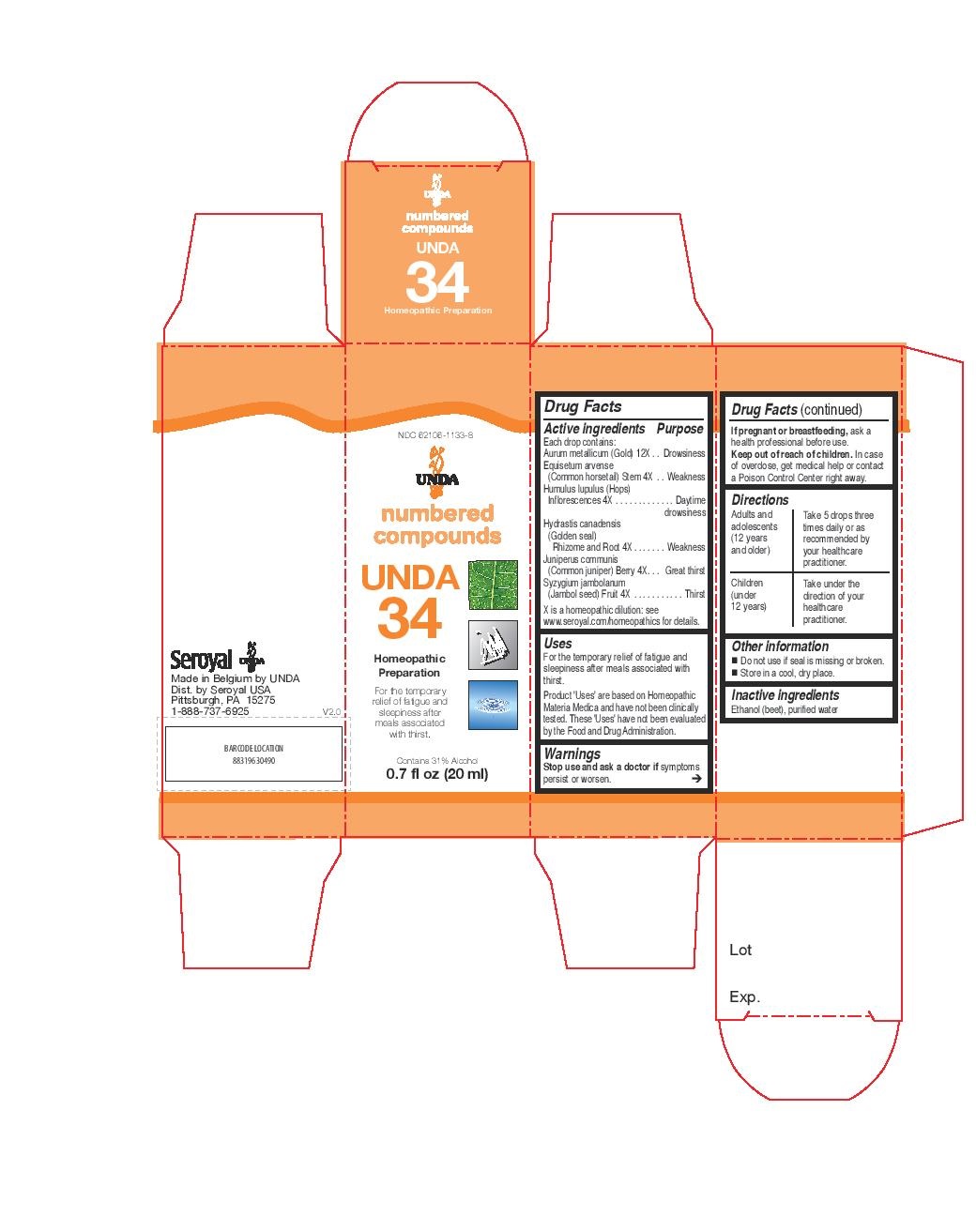 DRUG LABEL: UNDA 28
NDC: 62106-1127 | Form: LIQUID
Manufacturer: Seroyal USA
Category: homeopathic | Type: HUMAN OTC DRUG LABEL
Date: 20221109

ACTIVE INGREDIENTS: SARSAPARILLA 4 [hp_X]/20 mL; FILIPENDULA ULMARIA ROOT 4 [hp_X]/20 mL; ALUMINUM 12 [hp_X]/20 mL; COPPER 12 [hp_X]/20 mL; TIN 12 [hp_X]/20 mL; MARSDENIA CONDURANGO BARK 4 [hp_X]/20 mL; TARAXACUM OFFICINALE WHOLE 4 [hp_X]/20 mL; LACTUCA VIROSA 4 [hp_X]/20 mL
INACTIVE INGREDIENTS: WATER; ALCOHOL

UNDA numbers

Active ingredients
Each drop contains:
Aluminium metallicum (Aluminum) 12X
Condurango Bark 4X
Cuprum metallicum (Copper) 12X
Lactuca virosa (Poisonous lettuce) Whole Plant 4X
Sarsaparilla Root 4X
Spiraea ulmaria (Queen-of-the-meadow) Underground Parts 4X
Stannum metallicum (Tin) 12X
Taraxacum officinale (Common dandelion) Whole Plant 4X

Uses
For the temporary relief of minor joint, muscle and bone pain.

Warnings
Stop use and ask a doctor if symptoms
persist or worsen.
If pregnant or breastfeeding, ask a
health professional before use.
Keep out of reach of children. In case
of overdose, get medical help or contact
a Poison Control Center right away.

PREGNANCY OR BREAST FEEDING

If pregnant or breastfeeding, ask a health professional before use.

Keep out of reach of children.

OVERDOSAGE

In case of overdose, get medical help or contact a Poison Control Center right away.

Stop use and ask a doctor if symptoms persist or worsen.

Inactive Ingredients:

Ethanol (beet),
purified water

Other information
Do not use if seal is missing or broken.

Store in a cool, dry place.

Directions
Adults and adolescents (12 years and older)

Take 5 drops three times daily or as recommended by your healthcare practitioner.

Children (under 12 years)

Take under the direction of your healthcare practitioner.

Uses

For the temporary relief of minor joint, muscle and bone pain.

Directions
Adults and adolescents (12 years and older)

Take 5 drops three times daily or as recommended by your healthcare practitioner.

Children (under 12 years)

Take under the direction of your healthcare practitioner.

Active ingredients
Each drop contains:
Aurum metallicum (Gold) 12X
Equisetum arvense (Common horsetail) Stem 4X
Humulus lupulus (Hops) Inflorescences 4X
Hydrastis canadensis (Golden seal) Rhizome and Root 4X
Juniperus communis (Common juniper) Berry 4X
Syzygium jambolanum (Jambol seed) Fruit 4X

Uses
For the temporary relief of fatigue and sleepiness after meals associated with thirst.

Warnings
Stop use and ask a doctor if symptoms persist or worsen.
If pregnant or breastfeeding, ask a healthcare professional before use.
Keep out of reach of children.
In case of overdose, get medical help or contact a Poison Control Center right away.

PREGNANCY OR BREAST FEEDING

If pregnant or breastfeeding, ask a healthcare professional before use.

Keep out of reach of children.

OVERDOSAGE

In case of overdose, get medical help or contact a Poison Control Center right away.

Stop use and ask a doctor if symptoms persist or worsen.

Inactive Ingredients:

Ethanol (beet),
purified water

Other information
Do not use if seal is missing or broken.
Store in a cool, dry place.

Directions
Adults and adolescents (12 years and older)

Take 5 drops three times daily or as recommended by your healthcare practitioner.
Children (under 12 years)

Take under the direction of your healthcare practitioner.

Uses
For the temporary relief of fatigue and sleepiness after meals associated with thirst.

Directions
Adults and adolescents (12 years and older)

Take 5 drops three times daily or as recommended by your healthcare practitioner.
Children (under 12 years)

Take under the direction of your healthcare practitioner.

PACKAGE LABEL

NDC 62106-1127-8

UNDA

numbered compounds

UNDA 28

Homeopathic Preparation

For the temporary relief of minor joint,

muscle and bone pain.

Contains 31% Alcohol
0.7 fl oz (20 ml)

PACKAGE LABEL

NDC 62106-1133-8

UNDA

numbered compounds

UNDA 34

Homeopathic Preparation

For the temporary relief of fatigue and
sleepiness after meals associated with thirst.

Contains 31% Alcohol
0.7 fl oz (20 ml)